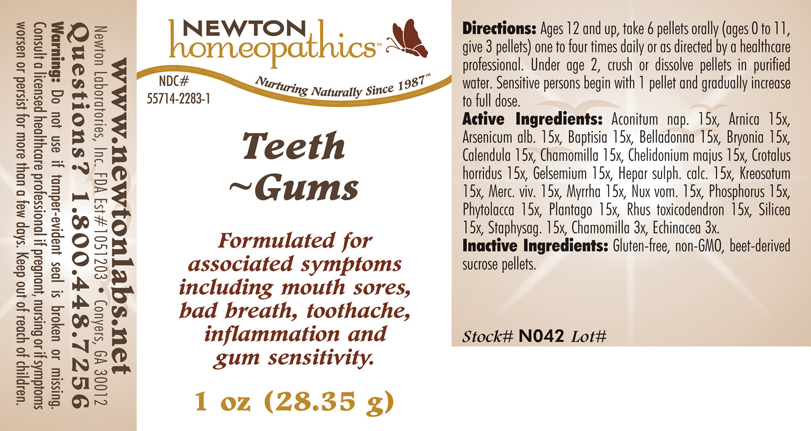 DRUG LABEL: Teeth - Gums 
NDC: 55714-2283 | Form: PELLET
Manufacturer: Newton Laboratories, Inc.
Category: homeopathic | Type: HUMAN OTC DRUG LABEL
Date: 20110301

ACTIVE INGREDIENTS: Aconitum Napellus 15 [hp_X]/1 g; Arnica Montana 15 [hp_X]/1 g; Arsenic Trioxide 15 [hp_X]/1 g; Baptisia Tinctoria 15 [hp_X]/1 g; Atropa Belladonna 15 [hp_X]/1 g; Bryonia Alba Root 15 [hp_X]/1 g; Calendula Officinalis Flowering Top 15 [hp_X]/1 g; Matricaria Recutita 15 [hp_X]/1 g; Chelidonium Majus 15 [hp_X]/1 g; Crotalus Horridus Horridus Venom 15 [hp_X]/1 g; Gelsemium Sempervirens Root 15 [hp_X]/1 g; Calcium Sulfide 15 [hp_X]/1 g; Wood Creosote 15 [hp_X]/1 g; Mercury 15 [hp_X]/1 g; Myrrh 15 [hp_X]/1 g; Strychnos Nux-vomica Seed 15 [hp_X]/1 g; Phosphorus 15 [hp_X]/1 g; Phytolacca Americana Root 15 [hp_X]/1 g; Plantago Major 15 [hp_X]/1 g; Toxicodendron Pubescens Leaf 15 [hp_X]/1 g; Silicon Dioxide 15 [hp_X]/1 g; Delphinium Staphisagria Seed 15 [hp_X]/1 g; Echinacea, Unspecified 3 [hp_X]/1 g
INACTIVE INGREDIENTS: Sucrose

Teeth - Gums

INDICATIONS & USAGE SECTION

Teeth - Gums Formulated for associated symptoms including mouth sores, bad breath, toothache, inflammation and gum sensitivity.

DOSAGE & ADMINISTRATION SECTION

Directions: Ages 12 and up, take 6 pellets orally (ages 0 to 11, give 3 pellets) one to four times daily or as directed by a healthcare professional. Under age 2, crush or dissolve pellets in purified water. Sensitive persons begin with 1 pellet and gradually increase to full dose.

OTC - ACTIVE INGREDIENT SECTION

Aconitum nap. 15x, Arnica 15x, Arsenicum alb. 15x, Baptisia 15x, Belladonna 15x, Bryonia 15x, Calendula 15x, Chamomilla 15x, Chelidonium majus 15x, Crotalus horridus 15x, Gelsemium 15x, Hepar sulph. calc. 15x, Kreosotum15x, Merc. viv. 15x, Myrrha 15x, Nux vom. 15x, Phosphorus 15x, Phytolacca 15x, Plantago 15x, Rhus toxicodendron 15x, Silicea 15x, Staphysag. 15x, Chamomilla 3x, Echinacea 3x.

OTC - PURPOSE SECTION

Formulated for associated symptoms including mouth sores, bad breath, toothache, inflammation and gum sensitivity.

INACTIVE INGREDIENT SECTION

Inactive Ingredients: Gluten-free, non-GMO, beet-derived sucrose pellets.

QUESTIONS SECTION

www.newtonlabs.net Newton Laboratories, Inc. FDA Est # 1051203 - Conyers, GA 30012
Questions? 1.800.448.7256

WARNINGS SECTION

Warning: Do not use if tamper - evident seal is broken or missing. Consult a licensed healthcare professional if pregnant, nursing or if symptoms worsen or persist for more than a few days. Keep out of reach of children.

OTC - PREGNANCY OR BREAST FEEDING SECTION

Consult a licensed healthcare professional if pregnant, nursing or if symptoms worsen or persist for more than a few days.

OTC - KEEP OUT OF REACH OF CHILDREN SECTION

Keep out of reach of children.